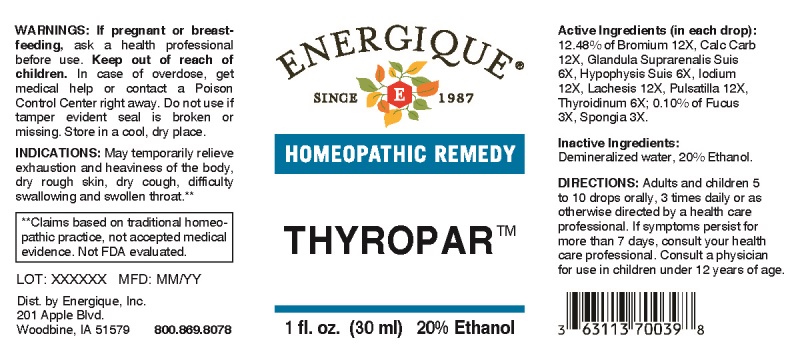 DRUG LABEL: Thyropar
NDC: 44911-0535 | Form: LIQUID
Manufacturer: Energique, Inc.
Category: homeopathic | Type: HUMAN OTC DRUG LABEL
Date: 20231030

ACTIVE INGREDIENTS: FUCUS VESICULOSUS 3 [hp_X]/1 mL; SPONGIA OFFICINALIS SKELETON, ROASTED 3 [hp_X]/1 mL; SUS SCROFA ADRENAL GLAND 6 [hp_X]/1 mL; SUS SCROFA PITUITARY GLAND 6 [hp_X]/1 mL; SUS SCROFA THYROID 6 [hp_X]/1 mL; BROMINE 12 [hp_X]/1 mL; OYSTER SHELL CALCIUM CARBONATE, CRUDE 12 [hp_X]/1 mL; IODINE 12 [hp_X]/1 mL; LACHESIS MUTA VENOM 12 [hp_X]/1 mL; ANEMONE PRATENSIS 12 [hp_X]/1 mL
INACTIVE INGREDIENTS: WATER; ALCOHOL

Drug Facts:

ACTIVE INGREDIENTS:

(in each drop): 12.48% of Bromium 12X, Calcarea Carbonica 12X, Glandula Suprarenalis (Suis) 6X, Hypophysis Suis 6X, Iodium 12X, Lachesis Mutus 12X, Pulsatilla (Pratensis) 12X, Thyroidinum (Suis) 6X; 0.10% of Fucus Vesiculosus 3X, Spongia Tosta 3X.

INDICATIONS:

May temporarily relieve exhaustion and heaviness of the body, dry rough skin, dry cough, difficulty swallowing and swollen throat.**

**Claims based on traditional homeopathic practice, not accepted medical evidence. Not FDA evaluated.

WARNINGS:

If pregnant or breast-feeding, ask a health professional before use.

Keep out of reach of children. In case of overdose, get medical help or contact a Poison Control Center right away.

Do not use if tamper evident seal is broken or missing.

Store in a cool, dry place.

Keep out of reach of children. In case of overdose, get medical help or contact a Poison Control Center right away.

DIRECTIONS:

Adults and children 5 to 10 drops orally, 3 times daily or as otherwise directed by a health care professional. If symptoms persist for more than 7 days, consult your health care professional. Consult a physician for use in children under 12 years of age.

INDICATIONS:

May temporarily relieve exhaustion and heaviness of the body, dry rough skin, dry cough, difficulty swallowing and swollen throat.**

**Claims based on traditional homeopathic practice, not accepted medical evidence. Not FDA evaluated.

INACTIVE INGREDIENTS:

Demineralized Water, 20% Ethanol

QUESTIONS:

Dist. by Energique, Inc.

201 Apple Blvd.

Woodbine, IA 51579 800.869.8078

PACKAGE LABEL DISPLAY:

ENERGIQUE
SINCE 1987
HOMEOPATHIC REMEDY
THYROPAR
1 fl. oz. (30 ml)